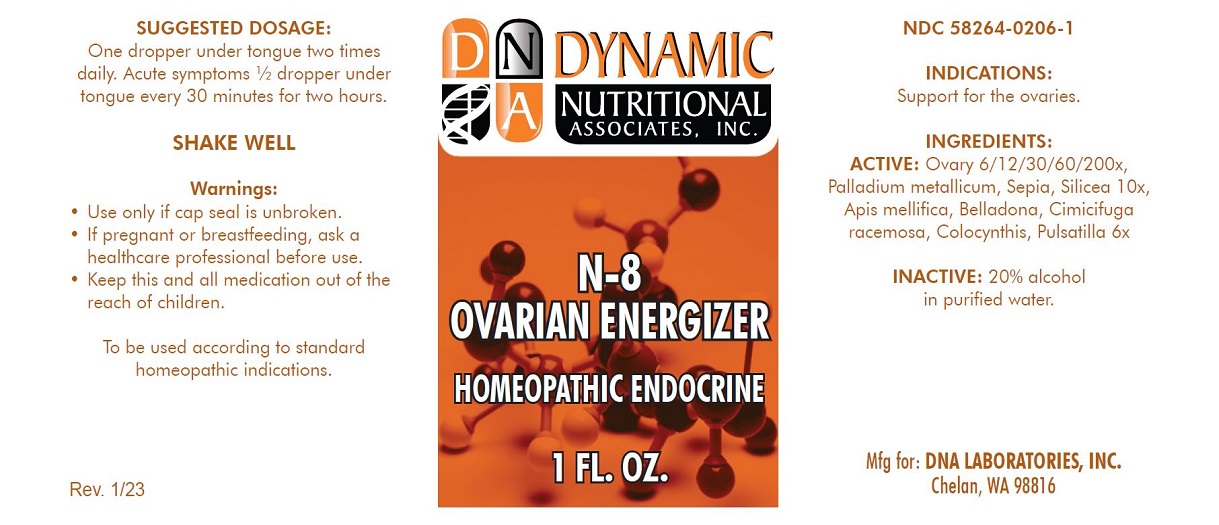 DRUG LABEL: N-8
NDC: 58264-0206 | Form: SOLUTION
Manufacturer: DNA Labs, Inc.
Category: homeopathic | Type: HUMAN OTC DRUG LABEL
Date: 20250109

ACTIVE INGREDIENTS: SILICON DIOXIDE 6 [hp_X]/1 mL; ATROPA BELLADONNA 6 [hp_X]/1 mL; CITRULLUS COLOCYNTHIS FRUIT PULP 6 [hp_X]/1 mL; BLACK COHOSH 6 [hp_X]/1 mL; ANEMONE PULSATILLA 6 [hp_X]/1 mL; SEPIA OFFICINALIS JUICE 10 [hp_X]/1 mL; PALLADIUM 10 [hp_X]/1 mL; APIS MELLIFERA 6 [hp_X]/1 mL; BOS TAURUS OVARY 200 [hp_X]/1 mL
INACTIVE INGREDIENTS: ALCOHOL; WATER

N-8

NDC 58264-0206-1

INDICATIONS

PURPOSE

Support for the ovaries.

ACTIVE INGREDIENT

INACTIVE INGREDIENT

Ovary 6/12/30/60/200x, Palladium metallicum, Sepia, Silicea 10x, Apis mellifica, Belladona, Cimicifuga racemosa, Colocynthis, Pulsatilla 6x, 20% alcohol in purified water.

SUGGESTED DOSAGE

One dropper under tongue two times daily. Acute symptoms ½ dropper under tongue every 30 minutes for two hours.

STORAGE AND HANDLING

SHAKE WELL

Warnings

- Use only if cap seal is unbroken.

PREGNANCY OR BREAST FEEDING

- As with drugs if you are pregnant or nursing a baby seek professional advice before using this product.

KEEP OUT OF REACH OF CHILDREN

- Keep this and all medication out of the reach of children.

To be used according to standard homeopathic indications.

PRINCIPAL DISPLAY PANEL - 1 FL. OZ. Bottle Label

DYNAMIC
NUTRITIONAL
ASSOCIATES, INC.

N-8
OVARIAN ENERGIZER

HOMEOPATHIC ENDOCRINE

1 FL. OZ.